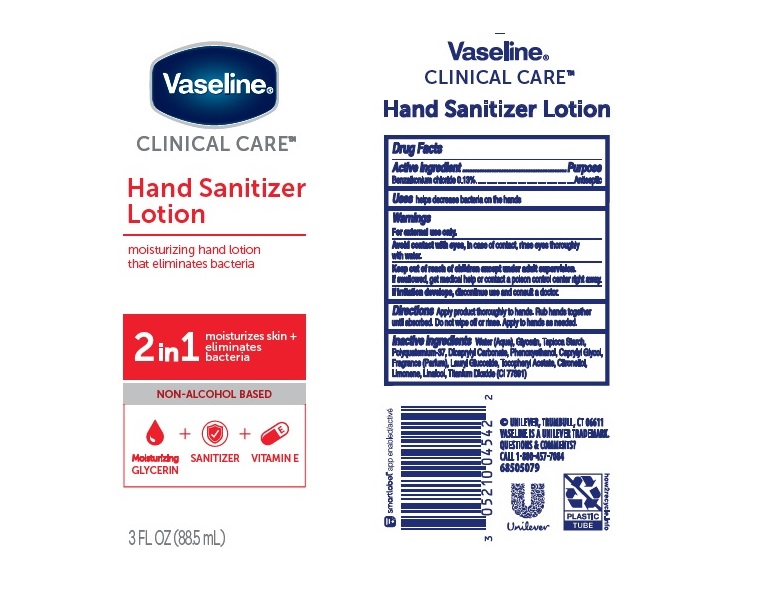 DRUG LABEL: Vaseline
NDC: 64942-1849 | Form: LOTION
Manufacturer: Conopco Inc. d/b/a/ Unilever
Category: otc | Type: HUMAN OTC DRUG LABEL
Date: 20241024

ACTIVE INGREDIENTS: BENZALKONIUM CHLORIDE 1.3 mg/1 mL
INACTIVE INGREDIENTS: STARCH, TAPIOCA; POLYQUATERNIUM-37 (10000 MPA.S); DICAPRYLYL CARBONATE; WATER; GLYCERIN; CAPRYLYL GLYCOL; LAURYL GLUCOSIDE; TITANIUM DIOXIDE; PHENOXYETHANOL; .ALPHA.-TOCOPHEROL ACETATE; .BETA.-CITRONELLOL, (R)-; LIMONENE, (+)-; LINALOOL, (+/-)-

Vaseline Clinical Care Hand Sanitizer Lotion

VASELINE CLINICAL CARE HAND SANITIZER LOTION - Benzalkonium Chloride lotion

Vaseline Clinical Care Hand Sanitizer Lotion

Drug Facts

Active ingredient

Benzalkonium Chloride 0.13%

Purpose

Antibacterial

Uses

helps decrease bacteria on the hands

Warnings

For external use only
Avoid contact with eyes, In case of contact, rinse eyes thoroughly with water.
If irritation develops, discontinue use and consult a doctor .

.

• Keep out of reach of children except under adult supervision.

If swallowed, get medical help or contact a poison control Center right away.

Directions

Apply product thoroughly to hands. Rub hands together until absorbed. Do not wipe off or rinse. Apply to hands as needed.

Inactive ingredients

Water (Aqua), Glycerin, Tapioca Starch, Polyquaternium-37, Dicaprylyl Carbonate, Phenoxyethanol, Caprylyl Glycol, Fragrance (Parfum), Lauryl Glucoside, Tocopheryl Acetate, Citronellol, Limonene, Linalool, Titanium Dioxide (CI 77891)

Questions or Comments?

1-800-457-7964

PACKAGE LABEL

Packaging